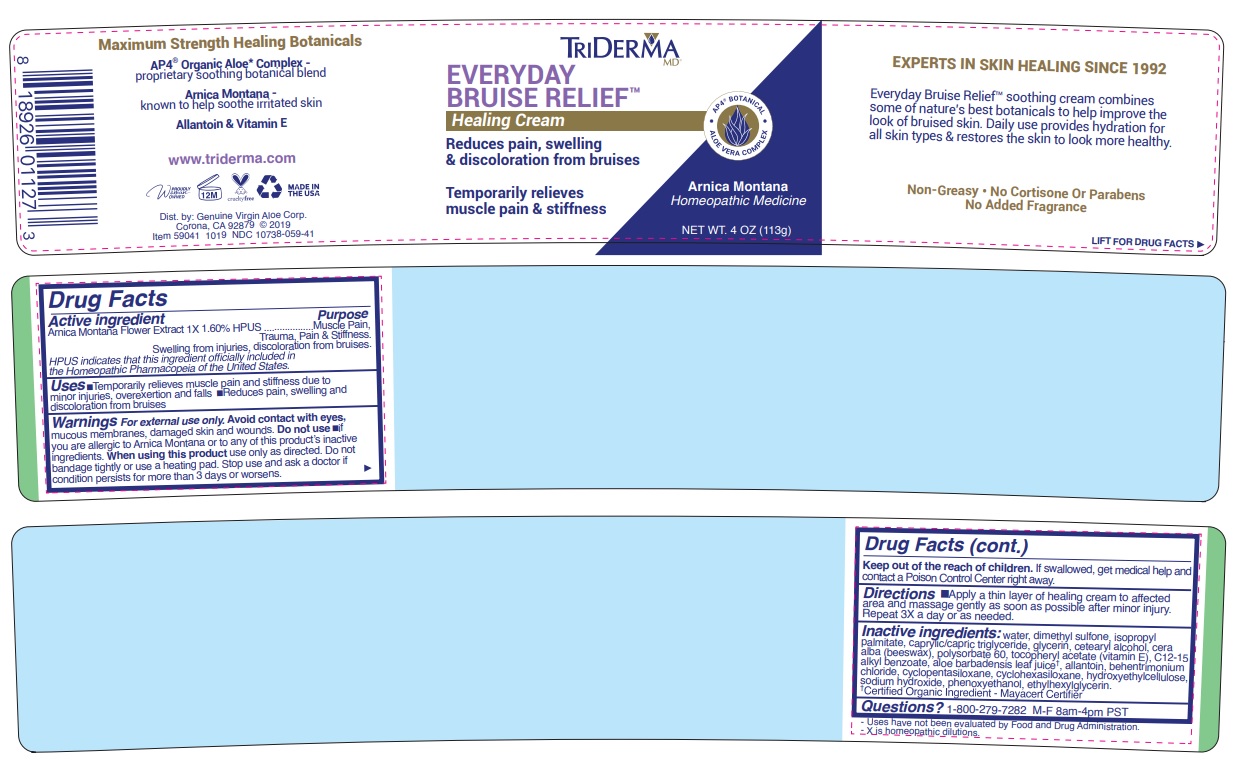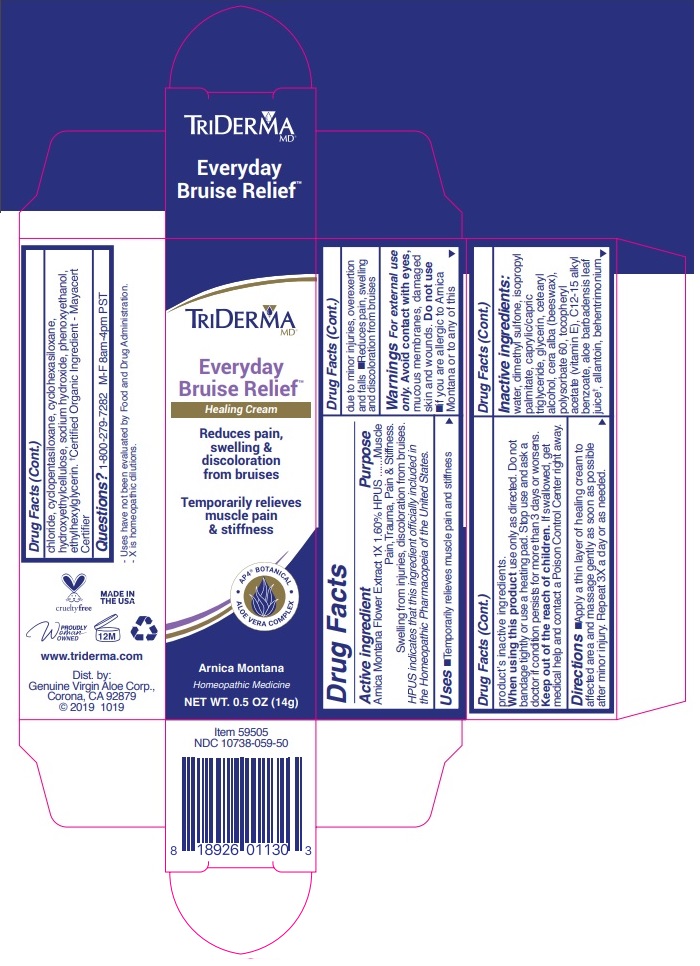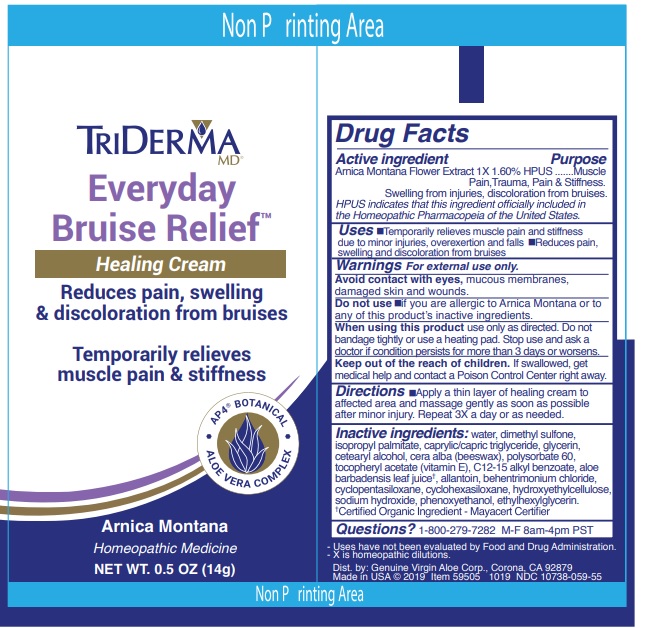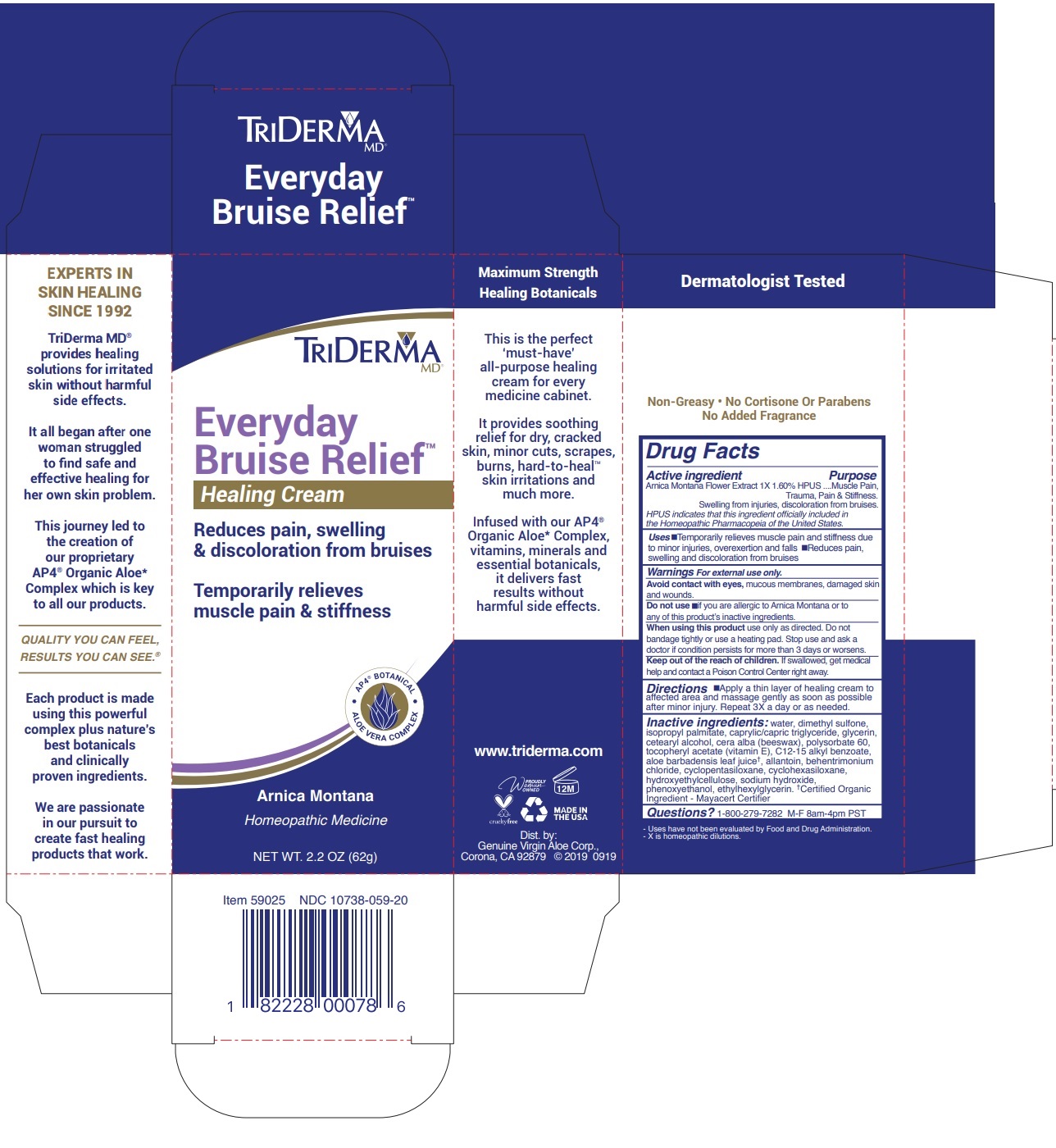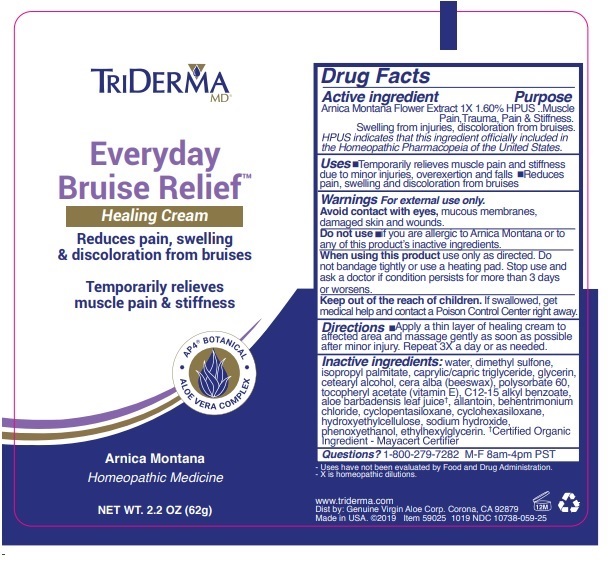 DRUG LABEL: TRIDERMA EVERYDAY BRUISE RELIEF
NDC: 10738-059 | Form: CREAM
Manufacturer: Genuine Virgin Aloe Corporation
Category: homeopathic | Type: HUMAN OTC DRUG LABEL
Date: 20260128

ACTIVE INGREDIENTS: ARNICA MONTANA 1.6 g/100 g
INACTIVE INGREDIENTS: WATER; DIMETHYL SULFONE; ISOPROPYL PALMITATE; MEDIUM-CHAIN TRIGLYCERIDES; GLYCERIN; CETOSTEARYL ALCOHOL; WHITE WAX; POLYSORBATE 60; .ALPHA.-TOCOPHEROL ACETATE; ALKYL (C12-15) BENZOATE; ALOE VERA LEAF; ALLANTOIN; BEHENTRIMONIUM CHLORIDE; CYCLOMETHICONE 5; CYCLOMETHICONE 6; HYDROXYETHYL CELLULOSE (100 MPA.S AT 2%); SODIUM HYDROXIDE; PHENOXYETHANOL; ETHYLHEXYLGLYCERIN

TRIDERMA Everyday Bruise Relief

Active ingredient

Arnica Montana Flower Extract 1X 1.60% HPUS

Purpose

Muscle Pain, Trauma, Pain & Stiffness.

Swelling from injuries, discoloration from bruises.

HPUS indicates that this ingredient officially included in the Homeopathic Pharmacopeia of the United States.

INDICATIONS AND USAGE

Uses •Temporarily relieves muscle pain and stiffness due to minor injuries, overexertion and falls •Reduces pain, swelling and discoloration from bruises

Warnings For external use only.

Avoid contact with eyes, mucous membranes, damaged skin and wounds.

Do not use •if you are allergic to Arnica Montana or to any of this product’s inactive ingredients.

When using this product use only as directed. Do not bandage tightly or use a heating pad. Stop use and ask a doctor if condition persists for more than 3 days or worsens.

KEEP OUT OF REACH OF CHILDREN

Keep out of the reach of children. If swallowed, get medical help and contact a Poison Control Center right away.

DOSAGE AND ADMINISTRATION

Directions •Apply a thin layer of healing cream to affected area and massage gently as soon as possible after minor injury. Repeat 3X a day or as needed.

INACTIVE INGREDIENT

Inactive ingredients: water, dimethyl sulfone, isopropyl palmitate, caprylic/capric triglyceride, glycerin, cetearyl alcohol, cera alba (beeswax), polysorbate 60, tocopheryl acetate (vitamin E), C12-15 alkyl benzoate, aloe barbadensis leaf juice†, allantoin, behentrimonium chloride, cyclopentasiloxane, cyclohexasiloxane, hydroxyethylcellulose, sodium hydroxide, phenoxyethanol, ethylhexylglycerin.†Certified Organic Ingredient - Mayacert Certifier

QUESTIONS

Questions? 1-800-279-7282 M-F 8am-4pm PST

Reduces pain, swelling & discoloration from bruises Temporarily relieves muscle pain & stiffness

AP4 BOTANICAL

ALOE VERA COMPLEX

Arnica Montana

Homeopathic Medicine

Maximum Strength

Healing Botanicals

This is the perfect ‘must-have’ all-purpose healing cream for every medicine cabinet.

It provides soothing relief for dry, cracked skin, minor cuts, scrapes, burns, hard-to-heal™ skin irritations and much more.

Infused with our AP4® Organic Aloe* Complex, vitamins, minerals and essential botanicals, it delivers fast results without harmful side effects

www.triderma.com

MADE IN THE USA

Dist. by: Genuine Virgin Aloe Corp.,

Corona, CA 92879 © 2019 0919

Dermatologist Tested

Non-Greasy • No Cortisone Or Parabens

No Added Fragrance

- Uses have not been evaluated by Food and Drug Administration.

- X is homeopathic dilutions.

EXPERTS IN SKIN HEALING SINCE 1992

TriDerma MD® provides healing solutions for irritated skin without harmful side effects.

It all began after one woman struggled to find safe and effective healing for her own skin problem.

This journey led to the creation of our proprietary AP4® Organic Aloe* Complex which is key to all our products.

QUALITY YOU CAN FEEL, RESULTS YOU CAN SEE.®

Each product is made using this powerful complex plus nature’s best botanicals and clinically proven ingredients.

We are passionate in our pursuit to create fast healing products that work.

Everyday Bruise Relief™ soothing cream combines some of nature’s best botanicals to help improve the look of bruised skin. Daily use provides hydration for all skin types & restores the skin to look more healthy.

Arnica Montana - known to help soothe irritated skin

Allantoin & Vitamin E